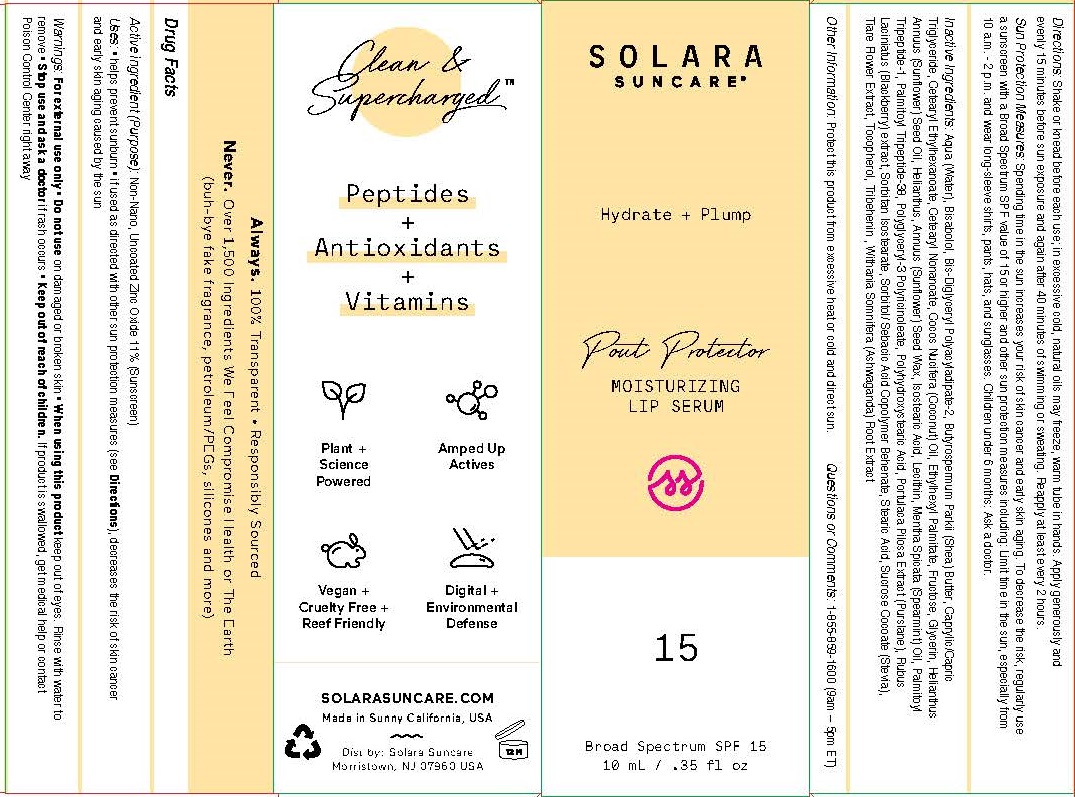 DRUG LABEL: SOLARA SUNCARE - POUT PROTECTOR

NDC: 73054-104 | Form: CREAM
Manufacturer: SOLARA SUNCARE, INC.
Category: otc | Type: HUMAN OTC DRUG LABEL
Date: 20251222

ACTIVE INGREDIENTS: ZINC OXIDE 11 g/100 mL
INACTIVE INGREDIENTS: ISOSTEARIC ACID; LECITHIN, SUNFLOWER; SPEARMINT OIL; PALMITOYL TRIPEPTIDE-1; PALMITOYL LYSYLDIOXYMETHIONYLLYSINE; WATER; .ALPHA.-BISABOLOL, (+/-)-; BIS-DIGLYCERYL POLYACYLADIPATE-2; SHEA BUTTER; MEDIUM-CHAIN TRIGLYCERIDES; CETEARYL ETHYLHEXANOATE; CETEARYL NONANOATE; COCONUT OIL; ETHYLHEXYL PALMITATE; FRUCTOSE; GLYCERIN; SUNFLOWER OIL; HELIANTHUS ANNUUS SEED WAX; POLYGLYCERYL-3 RICINOLEATE; POLYHYDROXYSTEARIC ACID (2300 MW); PORTULACA PILOSA WHOLE; RUBUS LACINIATUS WHOLE; SORBITAN ISOSTEARATE; SORBITOL; SEBACIC ACID; BEHENIC ACID; STEARIC ACID; SUCROSE COCOATE; GARDENIA TAITENSIS FLOWER; TOCOPHEROL; TRIBEHENIN; WITHANIA SOMNIFERA ROOT

SOLARA (as PLD) - POUT PROTECTOR SPF-15 (73054-104)

ACTIVE INGREDIENTS

Non-Nano, Non-Coated Zinc Oxide 20%

PURPOSE

Sunscreen

USES

- helps prevent sunburn
- if used as directed with other sun protection measures (see Directions), decreases the risk of skin cancer and early skin aging caused by the sun

WARNINGS

For external use only

Do not use on damaged or broken skin

When using this product keep out of eyes. Rinse with water to remove.

Stop use and ask a doctor if rash occurs

Keep out of reach of children. If product is swallowed, get medical help or contact Poison Control Center right away.

DIRECTIONS

- shake or knead before each use
- apply generously and evenly 15 minutes before sun exposure
- reapply:
- after 40 minutes of swimming or sweating
- immediately after towel drying
- at least every 2 hours

- Sun Protection Measures. Spending time in the sun increases your risk of skin cancer and early skin aging. To decrease the risk, regularly use asunscreen with a Broad Spectrum SPF value of 15 or higher and other sun protection measures including:
- limit time in the sun, especially from 10 a.m. - 2 p.m.
- wear long-sleeve shirts, pants, hats, and sunglasses
- children under 6 months: Ask a doctor

INACTIVE INGREDIENTS

Aqua (Water), Bisabolol, Bis-Diglyceryl Polyacyladipate-2, Butyrospermum Parkii (Shea) Butter, Caprylic/Capric Triglyceride, Cetearyl Ethylhexanoate, Cetearyl Nonanoate, Cocos Nucifera (Coconut) Oil, Ethylhexyl Palmitate, Fructose, Glycerin, Helianthus Annuus (Sunflower) Seed Oil, Helianthus, Annuus (Sunflower) Seed Wax, Isostearic Acid, Lecithin, Mentha Spicata (Spearmint) Oil, Palmitoyl Tripeptide-1, Palmitoyl Tripeptide-38, Polyglyceryl-3 Polyricinoleate, Polyhydroxystearic Acid, Portulaca Pilosa Extract (Purslane), Rubus Laciniatus (Blackberry) extract, Sorbitan Isostearate, Sorbitol/ Sebacic Acid Copolymer Behenate, Stearic Acid, Sucrose Cocoate (Stevia), Tiare Flower Extract, Tocopherol, Tribehenin , Withania Somnifera (Ashwaganda) Root Extract

OTHER INFORMATION

- Protect this product from excessive heat and direct sun.

QUESTIONS OR COMMENTS

- 1-855-859-1600 (9am – 5pm ET)